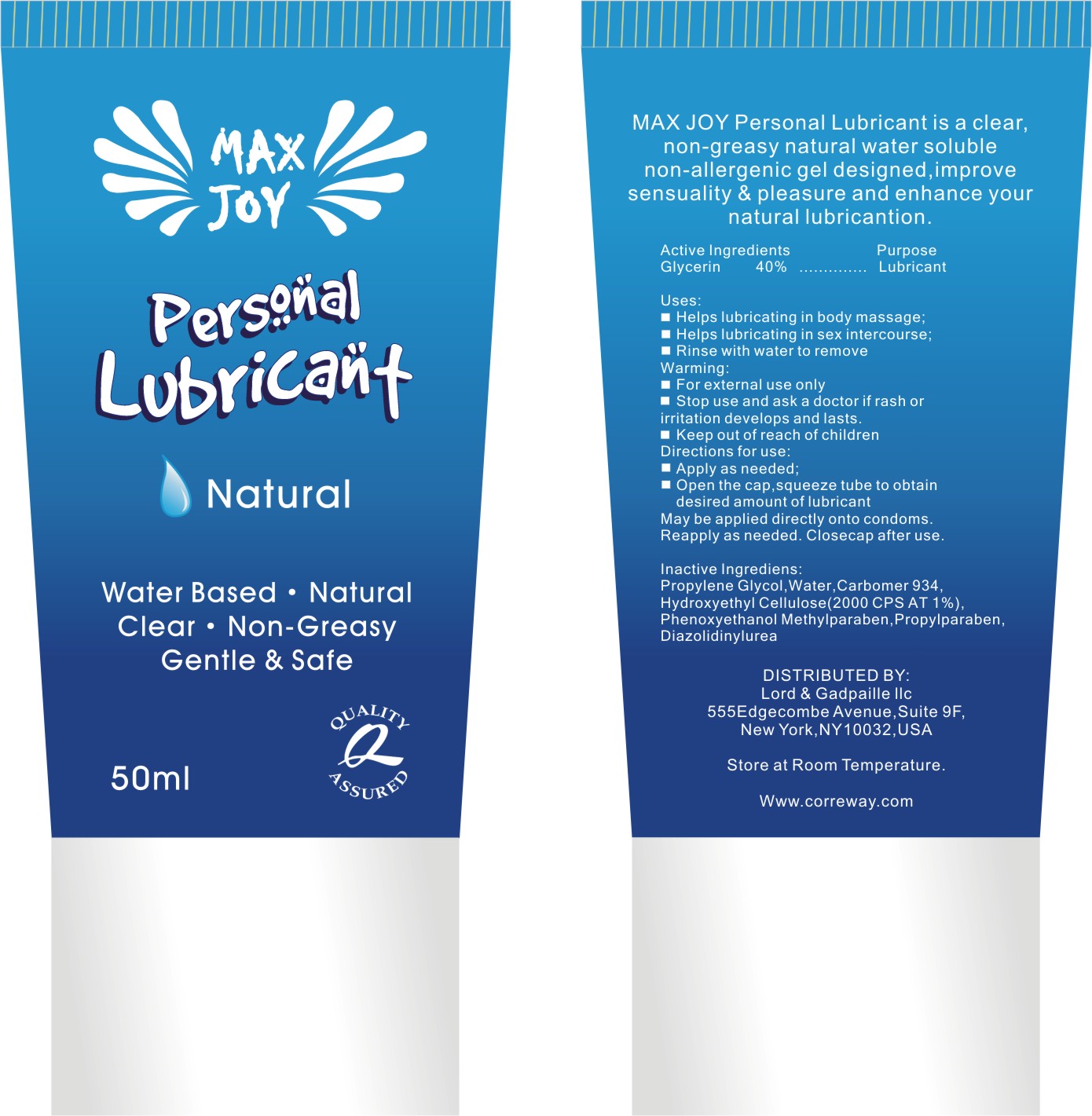 DRUG LABEL: Correway Personal Lubricant
NDC: 50600-001 | Form: JELLY
Manufacturer: Ningbo Correway Cosmetics Co., Ltd.
Category: otc | Type: HUMAN OTC DRUG LABEL
Date: 20100222

ACTIVE INGREDIENTS: Glycerin 19.312 g/48.28 g
INACTIVE INGREDIENTS: Propylene Glycol; Water; Carbomer 934; Hydroxyethyl Cellulose (2000 CPS AT 1%); Phenoxyethanol; Methylparaben; Propylparaben; Diazolidinylurea

Drug Facts

ACTIVE INGREDIENT

Glycerin

Stop use and ask a doctor if rash or irritation develops and lasts

Uses:
■ Helps lubricating in body massage;
■ Helps lubricating in sex intercourse;
■ Rinse with water to remove
Warning:
■ For external use only
■ Stop use and ask a doctor if rash or irritation develops and lasts.
■ Keep out of reach of children
Directions for use:
■ Apply as needed;
■ Open the cap,squeeze tube to obtain desired amount of lubricant. May be applied directly onto
condoms. Reapply as needed. Close cap after use.
Inactive Ingredients:
Propylene Glycol, Water, Carbomer 934, Hydroxyethyl Cellulose (2000 CPS AT 1%), Phenoxyethanol
Methylparaben, Propylparaben, Diazolidinylurea

PURPOSE

Helps lubricating in body massage;
Helps lubricating in sex intercourse;
Rinse with water to remove

Keep out of reach of children